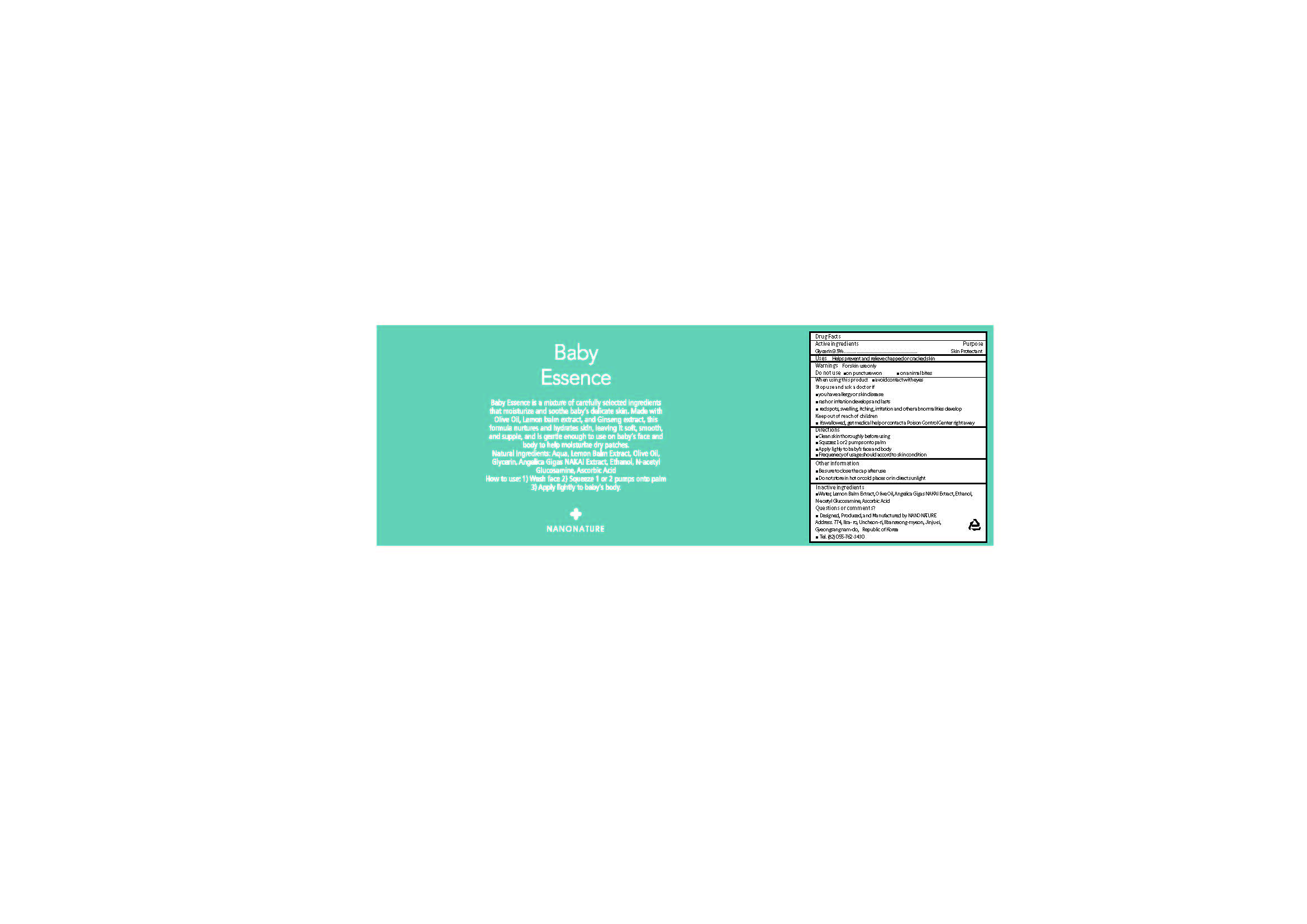 DRUG LABEL: Baby Essence
NDC: 71538-005 | Form: SOLUTION
Manufacturer: NANONATURE
Category: otc | Type: HUMAN OTC DRUG LABEL
Date: 20170717

ACTIVE INGREDIENTS: Glycerin 9.5 g/100 mL
INACTIVE INGREDIENTS: Water; Olive Oil; Tocopherol; Ascorbic Acid

ACTIVE INGREDIENT

Glycerin (9.5%) - Skin Protectant

INACTIVE INGREDIENT

Water, Lemon Balm Extract, Olive Oil, Angelica Gigas NAKAI Extract, Ethanol, N-acetyl Glucosamine, Ascorbic Acid

PURPOSE

Skin Protectant

WARNINGS

When using this product
 avoid contact with eyes
Stop use and ask a doctor if
 you have allergy or skin disease
 rash or irritation develops and lasts
 red spots, swelling, itching, irritation and other abnormalities develops

KEEP OUT OF REACH OF CHILDREN

 if swallowed, get medical help or contact a Poison Control Center right away

INDICATIONS & USAGE

 Clean skin thoroughly before using
 Squeeze 1 or 2 pumps onto palm
 Apply lightly to baby’s face and body
 Frequency of usage should accord to skin condition

DOSAGE & ADMINISTRATION

 Clean skin thoroughly before using
 Squeeze 1 or 2 pumps onto palm
 Apply lightly to baby’s face and body
 Frequency of usage should accord to skin condition